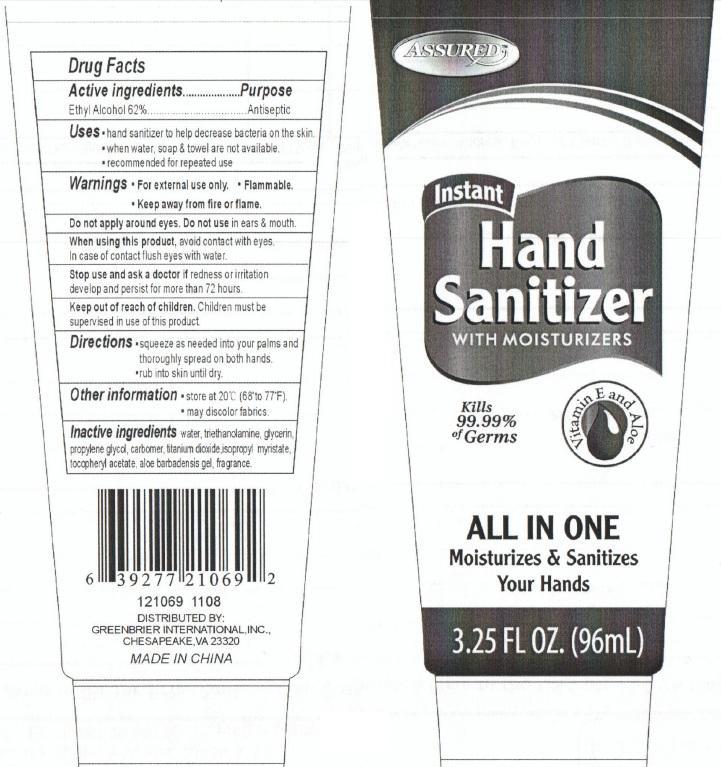 DRUG LABEL: INSTANT Hand Sanitizer with Moisturizers All In One
NDC: 33992-1069 | Form: GEL
Manufacturer: Greenbrier International, Inc.
Category: otc | Type: HUMAN OTC DRUG LABEL
Date: 20150218

ACTIVE INGREDIENTS: ALCOHOL 62 mL/100 mL
INACTIVE INGREDIENTS: WATER; TROLAMINE; GLYCERIN; PROPYLENE GLYCOL; TITANIUM DIOXIDE; ISOPROPYL MYRISTATE; .ALPHA.-TOCOPHEROL ACETATE, DL-; ALOE VERA LEAF

Instant Hand Sanitizer with Moisturizers All in One

Drug Facts

Active Ingredients

Ethyl Alcohol 62%

Purpose
Antiseptic

Uses

- Hand sanitizer to help decrease bacteria on the skin.
- When water, soap and towel are not available.
- Recommended for repeated use.

Warnings For external use only.

SAFE HANDLING WARNING

Flammable. Keep away from fire or flame.

WHEN USING

Do not apply around eyes. Do not use in ears and mouth

When using this product, avoid contact with eyes.

In case of contact flush eyes with water.

Stop use and ask a doctor if redness or irritation develop and persist for more than 72 hours.

Keep out of reach of children. Children must be supervised in use of this product.

Directions

- squeeze as needed into your palms and thoroughly spread on both hands

- rub into skin until dry.

Other Information

store at 20 degrees C (68 to 77 degrees F).

- may discolor fabrics.

Inactive Ingredients

water, triethanolamine, glycerin, propylene glycol, carbomer, titanium dioxide, isopropyl myristate, tocopheryl acetate, aloe barbadensis gel, fragrance

DESCRIPTION

Distributed By: GREENBRIAR INTERNATIONAL, INC.,

CHESAPEAKE, VA 23320

MADE IN CHINA

PACKAGE LABEL

Assured

INSTANT

Hand Sanitizer

with Moisturizers

Kills 99.99 percent of Germs!

ALL IN ONE

Moisturizes and Sanitizes Your Hands